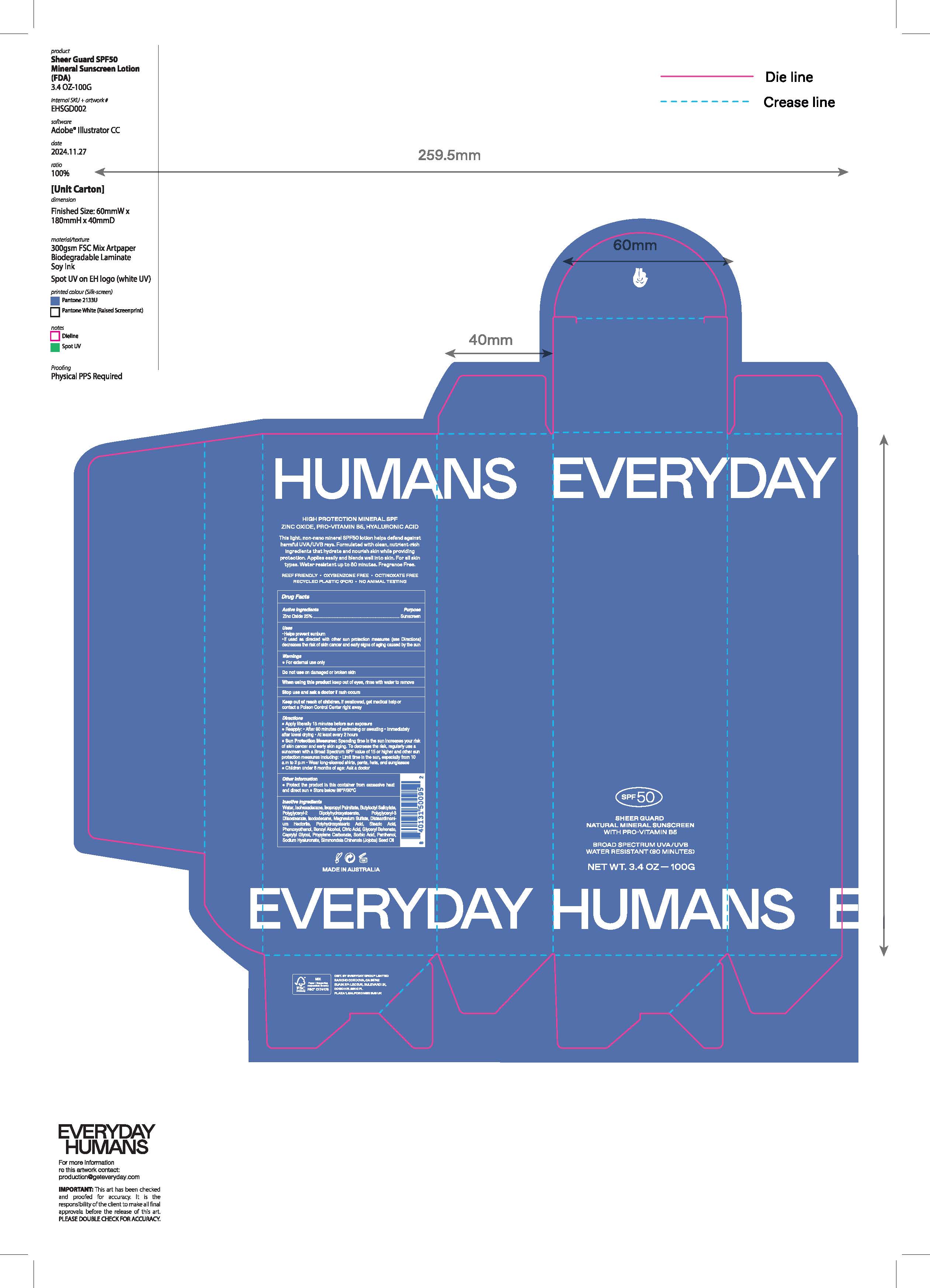 DRUG LABEL: Sheer Guard Natural Mineral Sunscreen Broad Spectrum SPF 50
NDC: 70157-028 | Form: CREAM
Manufacturer: Baxter Laboratories Pty
Category: otc | Type: HUMAN OTC DRUG LABEL
Date: 20250902

ACTIVE INGREDIENTS: ZINC OXIDE 25 g/100 g
INACTIVE INGREDIENTS: PROPYLENE CARBONATE; DISTEARDIMONIUM HECTORITE; CITRIC ACID; SODIUM HYALURONATE; ISOPROPYL PALMITATE; POLYGLYCERYL-3 DIISOSTEARATE; MAGNESIUM SULFATE; STEARIC ACID; CAPRYLYL GLYCOL; BUTYLOCTYL SALICYLATE; ISOHEXADECANE; POLYGLYCERYL-2 DIPOLYHYDROXYSTEARATE; BENZYL ALCOHOL; JOJOBA OIL; GLYCERYL DIBEHENATE; SORBIC ACID; WATER; PANTHENOL; ISODODECANE; POLYHYDROXYSTEARIC ACID (2300 MW); PHENOXYETHANOL

Sheer Guard Natural Mineral Sunscreen Broad Spectrum SPF 50

Active ingredients purpose

Zinc Oxide 25%.....Sunscreen

Uses

- Helps prevent sunburn
- If used as directed with other sun protection measures (see

Directions), decreases the risk of skin cancer and early skin aging

caused by the sun.

Keep out of reach of children. If Product is swallowed, get medical help or contact a Poison Control Center right away.

Stop use and ask a doctor if rash occurs

Warnings

For External Use Only

Do not use on damaged or broken skin

When using this product keep out of eyes. Rinse with water to

Directions

- Apply liberally 15 minutes before sun exposure
- Reapply:
- after 80 minutes of swimming or sweating
- Immediately after towel drying
- At least every 2 hours
- Sun Protection Measures. Spending time in the sun increases your risk of skin cancer and early skin aging. To decrease this risk, regularly use a sunscreen with a Broad Spectrum SPF value 15 or higher and other sun protection measures including:
- Limit time in the sun, especially from 10a.m. – 2p.m.
- Wear long-sleeve shirts, pants, hats, and sunglasses
- Children under 6 months: Ask a doctor

Inactive ingredients

Water, Isohexadecane, Isopropyl Palmitate, Butyloctyl Salicylate, Polyglyceryl-2 Dipolyhydroxstearate, Polyglyceryl-3 Diisostearate, Isododecane, Magnesium Sulfate, Disteardimonium Hectorite, Polyhydroxystearic Acid, Stearic Acid, Phenoxyethanol, Benzyl Alcohol, Citric Acid, Glyceryl Behenate, Caprylyl Glycol, Propylene Carbonate, Sorbic Acid, Panthenol, Sodium Hyaluronate, Simmondsia Chinenesis (Jojoba) Seed Oil

PACKAGE LABEL

Everyday Humans

SPF 50

Sheer Guard Natural Mineral Suunscreen

with pro-vitamin B5

Broad Spectrum UVA/UVB

Water Resistant (80 minutes)

Net Wt. 3.4 OZ 100G